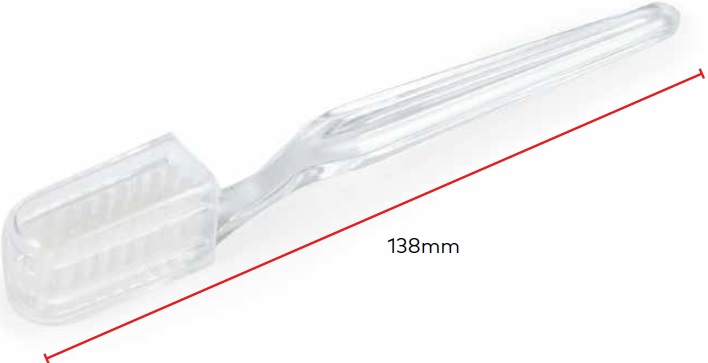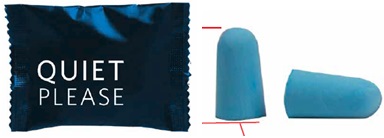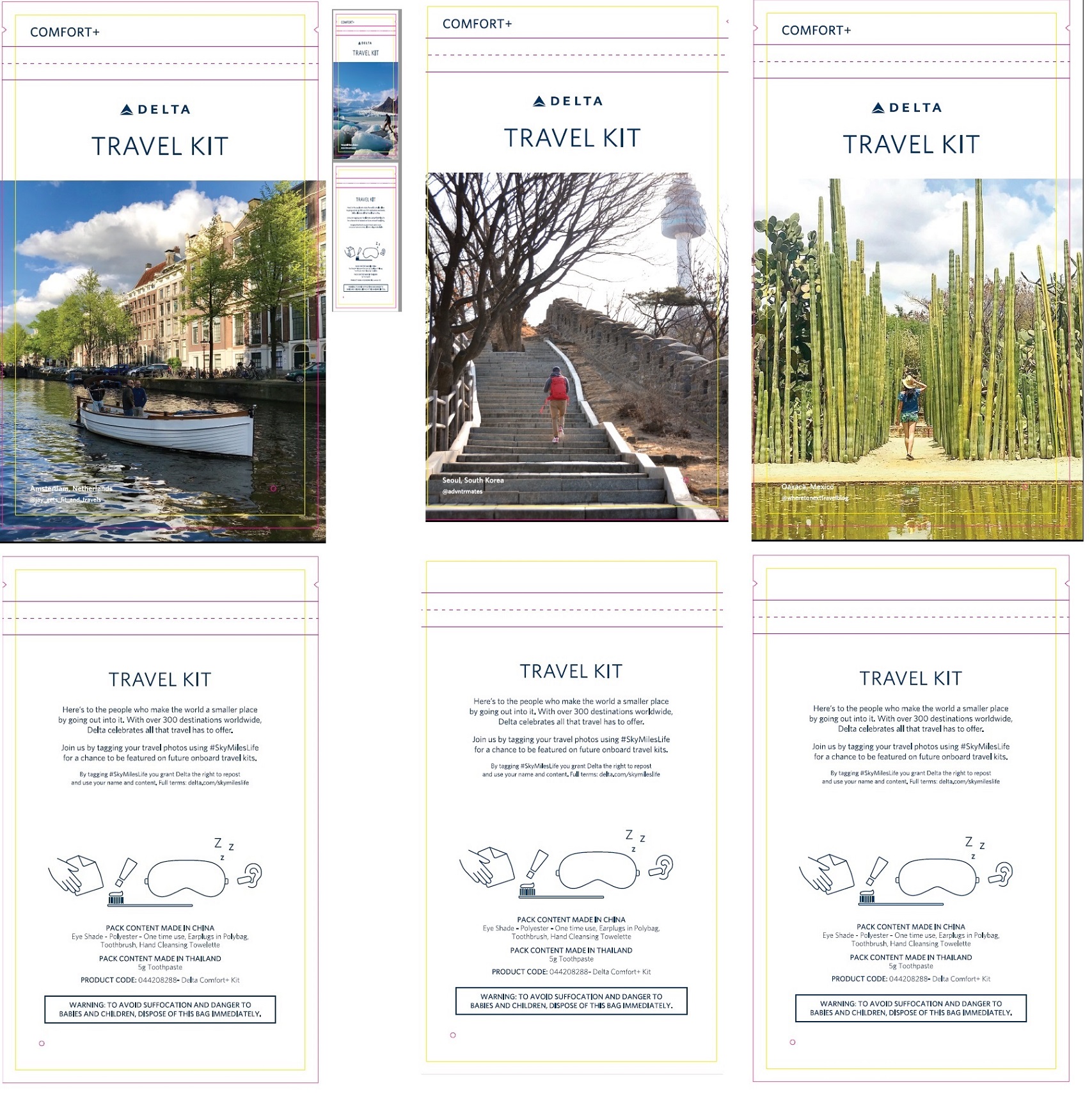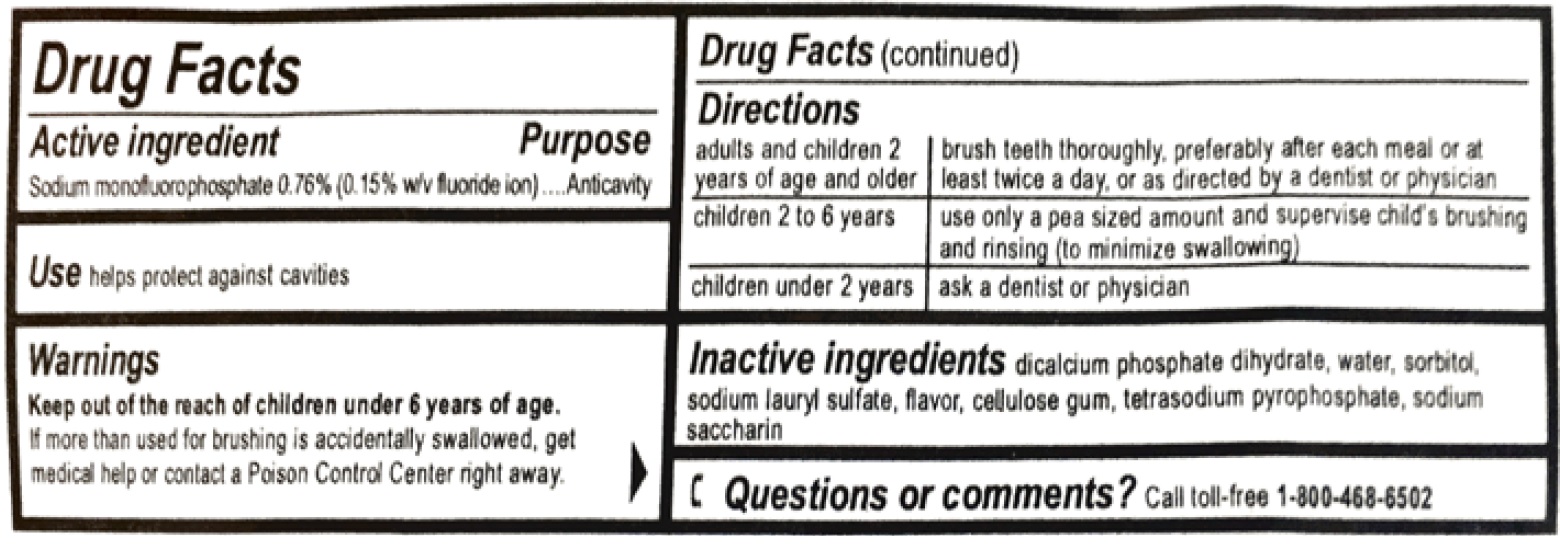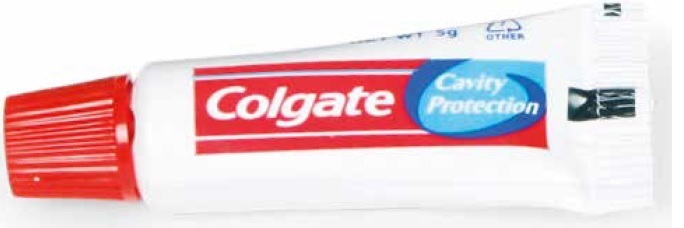 DRUG LABEL: DELTA COMFORT PLUS AMENITY
NDC: 69491-043 | Form: KIT | Route: DENTAL
Manufacturer: Buzz Products Inc.
Category: otc | Type: HUMAN OTC DRUG LABEL
Date: 20251218

ACTIVE INGREDIENTS: SODIUM MONOFLUOROPHOSPHATE 7.6 mg/1 g
INACTIVE INGREDIENTS: DIBASIC CALCIUM PHOSPHATE DIHYDRATE; WATER; SORBITOL; SODIUM LAURYL SULFATE; METHYL SALICYLATE; CARBOXYMETHYLCELLULOSE SODIUM, UNSPECIFIED FORM; SODIUM PYROPHOSPHATE; SACCHARIN SODIUM

DELTA COMFORT PLUS - AMENITY KIT

Active ingredient

Sodium monofluorophosphate 0.76% (0.15% w/v fluoride ion)

Purpose

Anticavity

Use

helps protect against cavities

Warnings

Keep out of the reach of children under 6 years of age.

If more than used for brushing is accidentally swallowed, get medical help or contact a Poison Control Center right away.

Directions

adults and children 2 years of age and older | brush teeth thoroughly, preferably after each meal or at least twice a day, or as directed by a dentist or physician
children 2 to 6 years | use only apea sized amount and supervise child's brushing and rinsing (to minimize swallowing)
children under 2 years | ask a dentist or physician

Inactive ingredients

dicalcium phosphate dihydrate, water, sorbitol, sodium lauryl sulfate, flavor, cellulose gum, tetrasodium pyrophosphate, sodium saccharin

Questions or comments?

1-800-492-7378